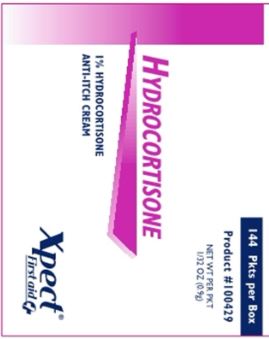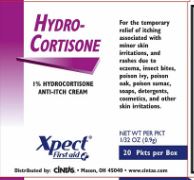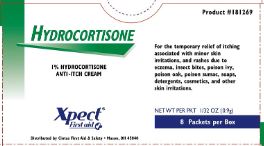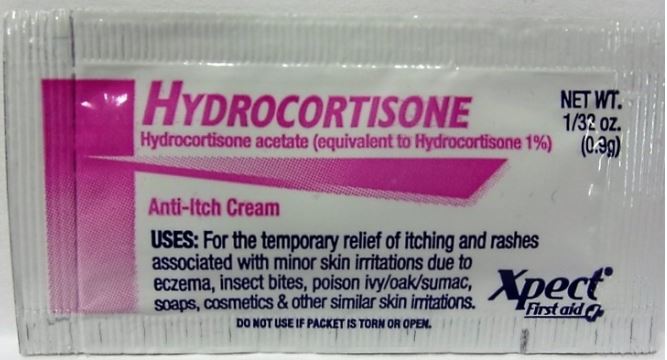 DRUG LABEL: Xpect Hydrocortisone
NDC: 42961-220 | Form: CREAM
Manufacturer: Cintas Corp
Category: otc | Type: HUMAN OTC DRUG LABEL
Date: 20250926

ACTIVE INGREDIENTS: HYDROCORTISONE ACETATE 0.01 g/1 g
INACTIVE INGREDIENTS: CETYL ALCOHOL; CITRIC ACID MONOHYDRATE; DIAZOLIDINYL UREA; EDETATE DISODIUM ANHYDROUS; GLYCERIN; GLYCERYL MONOSTEARATE; METHYLPARABEN; MINERAL OIL; POLYETHYLENE GLYCOL, UNSPECIFIED; PROPYLENE GLYCOL; PROPYLPARABEN; WATER; STEARIC ACID; TROLAMINE

Active ingredients (in each packet)

Hydrocortisone acetate 1%

Purpose

anti-itch cream

Uses

temporarily relieves itching associated with minor skin irritations and rashes due to:

- eczema
- insect bites
- poison ivy, oak, or sumac
- soaps, detergents, or cosmetics
- jewelry

Warnings

For external use only

Do not use

- with any other hydrocortisone product unless you have consulted a doctor
- for the treatment of diaper rash, consult a doctor

When using this product

- avoid contact with eyes

Stop use and ask a doctor if

- condition worsens
- symptoms persist for more than 7 days
- symptoms clear up and occur again within a few days

Keep out of reach of children.

If swallowed, get medical help or contact a Poison Control Center right away.

Directions

adults and children; 2 years and over | apply to affected area not more; than 3 to 4 times daily
children under 2 years | do not use, consult a physician

Other information

- do not use if package is torn, cut or opened
- store at room temperature (do not freeze)
- see packet for Lot Number and expiration date

Inactive Ingredients

cetyl alcohol, citric acid, diazolidinyl urea, edetate disodium, glycerin, glyceryl monosterate, methylparaben, mineral oil, polyethylene glycol, propylene glycol, propylparaben, purified water, stearic acid, trolamine

Questions?

1-877-973-2811 Monday-Friday 8:00am-5:00pm

Principal Display Panel - Packet

HYDROCORTISONE

Hydrocortisone acetate (equivalent to Hydrocortisone 1%)

NET WT. 1/32 oz. (0.9g)

Anti-Itch Cream

USES: For the temporary relief of itching and rashes associated with minor skin irritations due to eczema, insect bites, poison ivy/oak/sumac, soaps, cosmetics & other similar skin irritations.

DO NOT USE IF PACKET IS TORN OR OPEN.

Xpect® First aid

Principal Display Panel - 8 Count Box

HYDROCORTISONE

1% HYDROCORTISONE ANTI-ITCH CREAM

Xpect® First aid

Distributed by Cintas First Aid & Safety • Mason, OH 45040

Product #181269

For the temporary relief of itching associated with minor skin irritations and rashes due to eczema, insect bites, poison ivy, poison oak, poison sumac, soaps, detergents, cosmetics, and other skin irritations.

NET WT PER PKT 1/32 OZ (0.9g)

8 Packets per Box

Principal Display Panel - 20 Count Box

HYDRO-CORTISONE

1% HYDROCORTISONE ANTI-ITCH CREAM

Xpect® First aid

Distributed by: Cintas • Mason, OH 45040 • www.cintas.com

For the temporary relief of itching associated with minor skin irritations, and rashes due to eczema, insect bites, poison ivy, poison oak, poison sumac, soaps, detergents, cosmetics, and other skin irritations.

NET WT PER PKT

1/32 OZ (0.9g)

20 Pkts per Box

Principal Display Panel - 144 Count Box

144 Pkts per Box

Product #100429

NET WT PER PKT

1/32 OZ (0.9g)

HYDROCORTISONE

1% HYDROCORTISONE ANTI-ITCH CREAM

Xpect® First aid